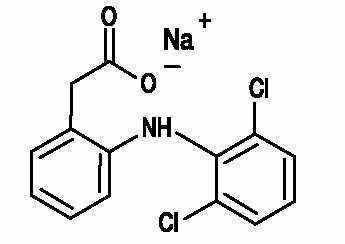 DRUG LABEL: Unknown
Manufacturer: FALCON Pharmaceuticals, Ltd.
Category: prescription | Type: Human Prescription Drug Label
Date: 20060703

Diclofenac Sodium
Ophthalmic Solution, 0.1%

DESCRIPTION

Diclofenac Sodium Ophthalmic Solution, 0.1% is a sterile, topical, nonsteroidal, anti-inflammatory product for ophthalmic use. Diclofenac sodium is designated chemically as 2-[(2,6-dichlorophenyl)amino] benzeneacetic acid, monosodium salt, with an empirical formula of C14H10Cl2NO2Na. The structural formula of diclofenac sodium is:

Diclofenac Sodium Ophthalmic Solution, 0.1% is available as a sterile solution which contains diclofenac sodium 0.1% (1 mg/mL).

Inactive Ingredients: POLYQUAD® polyquaternium-1, 0.05 mg/mL, as preservative, tocophersolan, boric acid, mannitol, hydrochloric acid and/or sodium hydroxide (to adjust pH to 6.7) and purified water. DM-00

Diclofenac sodium is a faintly yellow-white to light-beige, slightly hygroscopic crystalline powder. It is freely soluble in methanol, sparingly soluble in water, very slightly soluble in acetonitrile, and insoluble in chloroform and in 0.1N hydrochloric acid. Its molecular weight is 318.14. Diclofenac Sodium Ophthalmic Solution, 0.1% is an iso-osmotic solution with an osmolality of about 300 mOsmol/1000g.

CLINICAL PHARMACOLOGY

Animal Studies

Prostaglandins have been shown in many animal models to be mediators of certain kinds of intraocular inflammation. In studies performed in animal eyes, prostaglandins have been shown to produce disruption of the blood-aqueous humor barrier, vasodilation, increased vascular permeability, leukocytosis, and increased intraocular pressure.

Pharmacodynamics

Diclofenac sodium is one of a series of phenylacetic acids that have demonstrated anti-inflammatory and analgesic properties in pharmacological studies. It is thought to inhibit the enzyme cyclooxygenase, which is essential in the biosynthesis of prostaglandins.

Pharmacokinetics

Results from a bioavailability study of another formulation of diclofenac sodium ophthalmic solution established that plasma levels of diclofenac following ocular instillation of two drops of diclofenac sodium ophthalmic solution, 0.1% to each eye were below the limit of quantitation (10 ng/mL) over a 4-hour period. This study suggests that limited, if any, systemic absorption occurs with diclofenac sodium ophthalmic solution, 0.1%.

Clinical Trials

Postoperative Anti-Inflammatory Effects

In a clinical therapeutic equivalence study, Diclofenac Sodium Ophthalmic Solution, 0.1%, was found to be therapeutically equivalent to VOLTAREN OPHTHALMIC® (diclofenac sodium ophthalmic solution) [CIBA VISION OPHTHALMICS®] in the treatment of signs and symptoms of inflammation resulting from cataract surgery.

INDICATIONS AND USAGE

Diclofenac Sodium Ophthalmic Solution, 0.1% is indicated for the treatment of postoperative inflammation in patients who have undergone cataract extraction.

CONTRAINDICATIONS

Diclofenac Sodium Ophthalmic Solution, 0.1% is contraindicated in patients who are hypersensitive to any component of the medication.

WARNINGS

With some nonsteroidal anti-inflammatory drugs, there exists the potential for increased bleeding time due to interference with thrombocyte aggregation. There have been reports that ocularly applied nonsteroidal anti-inflammatory drugs may cause increased bleeding of ocular tissues (including hyphemas) in conjunction with ocular surgery.

There is the potential for cross-sensitivity to acetylsalicylic acid, phenylacetic acid derivatives, and other non-steroidal anti-inflammatory agents. Therefore, caution should be used when treating individuals who have previously exhibited sensitivities to these drugs.

PRECAUTIONS

General

It is recommended that Diclofenac Sodium Ophthalmic Solution, 0.1%, like other NSAIDs, be used with caution in surgical patients with known bleeding tendencies or who are receiving other medications that may prolong bleeding time.

Diclofenac Sodium Ophthalmic Solution, 0.1% may slow or delay healing.

Results from clinical studies indicate that Diclofenac Sodium Ophthalmic Solution, 0.1% has no significant effect upon intraocular pressure, however, elevations in intraocular pressure may occur following cataract surgery.

Carcinogenesis, Mutagenesis, Impairment of Fertility

Long term carcinogenicity studies in rats given oral diclofenac sodium up to 2 mg/kg/day (approximately the human oral dose) have revealed no significant increases in tumor incidence. There was a slight increase in benign rat mammary fibroadenomas in mid-dose females (high dose females had excessive mortality) but the increase was not significant for this common rat tumor. A 2-year carcinogenicity study conducted in mice employing oral diclofenac sodium up to 2 mg/kg/day did not reveal any oncogenic potential. Diclofenac sodium did not show mutagenic potential in various mutagenicity studies including the Ames test. Diclofenac sodium administered to male and female rats at 4 mg/kg/day did not affect fertility.

Pregnancy

Teratogenic Effects

Pregnancy Category C. Reproduction studies performed in mice at oral doses up to 5000 times (20 mg/kg/day) and in rats and rabbits at oral doses up to 2500 times (10 mg/kg/day) the human topical dose have revealed no evidence of teratogenicity due to diclofenac sodium, despite the induction of maternal toxicity and fetal toxicity. In rats, maternally toxic doses were associated with dystocia, prolonged gestation, reduced fetal weights and growth, and reduced fetal survival. Diclofenac sodium has been shown to cross the placental barrier in mice and rats.

There are however, no adequate and well-controlled studies in pregnant women. Because animal reproduction studies are not always predictive of human response, this drug should be used during pregnancy only if clearly needed.

Nonteratogenic effects

Because of the known effects of prostaglandin biosynthesis-inhibiting drugs on the fetal cardiovascular system (closure of the ductus arteriosus), the use of Diclofenac Sodium Ophthalmic Solution, 0.1% during late pregnancy should be avoided.

Pediatric Use

Safety and effectiveness in pediatric patients have not been established.

ADVERSE REACTIONS

Ocular

Transient burning and stinging was reported in 15% of patients with the use of topical diclofenac sodium ophthalmic solution, 0.1%. In cataract studies, keratitis occurred in 28% of patients receiving diclofenac sodium ophthalmic solution, 0.1%; however, most of the cases of keratitis occurred prior to drug therapy. Elevated intraocular pressure was reported in 15% of patients receiving diclofenac sodium ophthalmic solution, 0.1%. The following adverse reactions were reported in approximately 5% or less of the patients: abnormal vision, anterior chamber reaction, blurred vision, conjunctivitis, corneal deposits, corneal edema, corneal lesions, corneal opacity, discharge, injection, iritis, irritation, itching and ocular allergy.

Systemic

The following adverse reactions were reported in 3% or less of the patients: abdominal pain, asthenia, chills, dizziness, facial edema, fever, headache, insomnia, nausea, pain, rhinitis, viral infection, and vomiting.

OVERDOSAGE

Overdosage will not ordinarily cause acute problems. If accidentally ingested, fluids should be taken to dilute the medication.

DOSAGE AND ADMINISTRATION

One drop of Diclofenac Sodium Ophthalmic Solution, 0.1% should be applied to the affected eye four times daily beginning 24 hours after cataract surgery and continuing throughout the first 2 weeks of the postoperative period.

How Supplied

Diclofenac Sodium Ophthalmic Solution, 0.1% is supplied in opaque, plastic DROP-TAINER® dispenser in the following sizes:

2.5 mL: NDC 61314-231-26

5.0 mL: NDC 61314-231-05

Store between 59° -86° F (15° -30° C). Protect from light. Dispense in original, unopened container only.

Rx Only

U.S. Patent Nos. 5,603,929 and 5,653,972

Distributed by:
FALCON Pharmaceuticals, Ltd.
Fort Worth, Texas 76134 USA

Manufactured by:
ALCON LABORATORIES, INC.
Fort Worth, Texas 76134 USA

February 1999

342458-0299